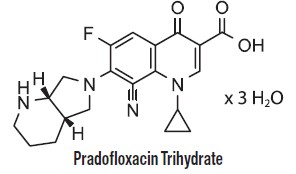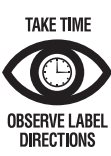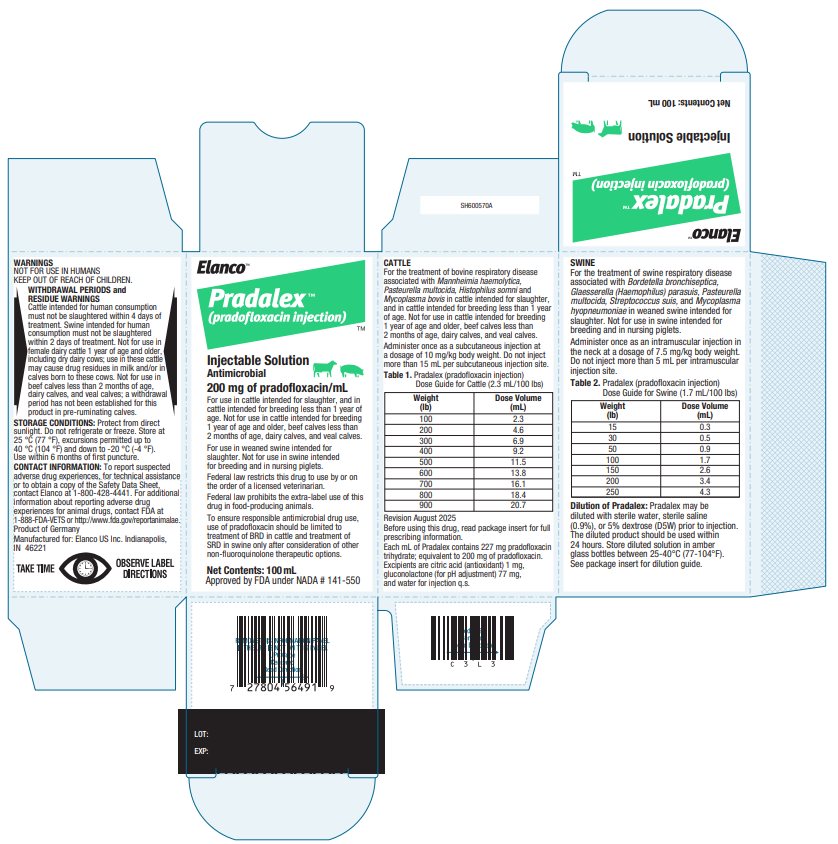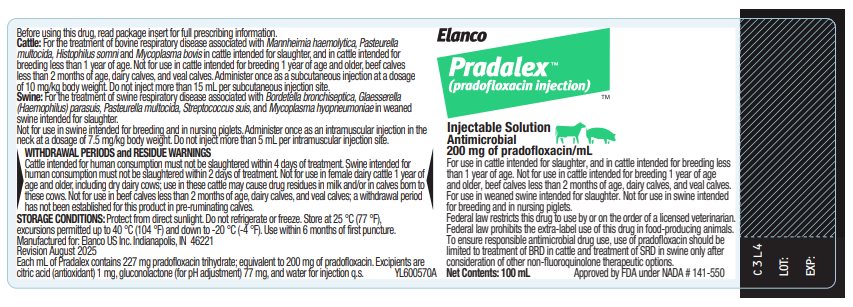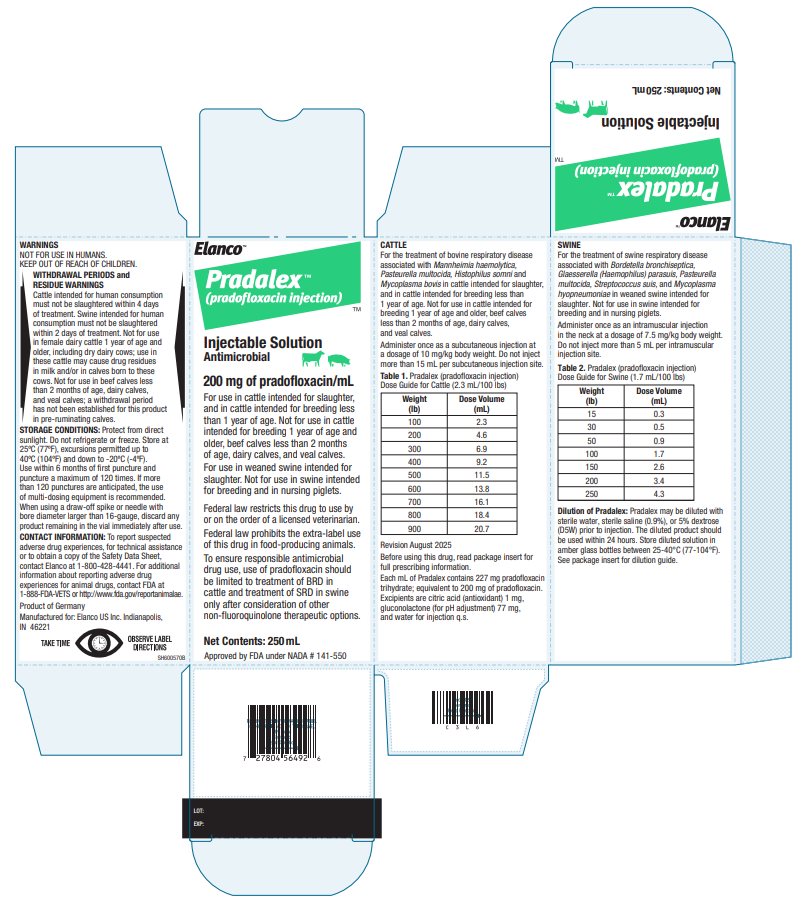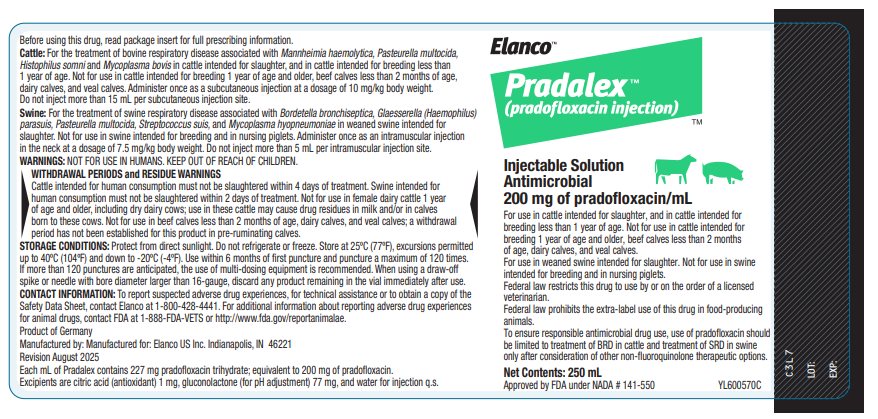 DRUG LABEL: Pradalex
NDC: 58198-8527 | Form: INJECTION, SOLUTION
Manufacturer: Elanco US Inc.
Category: animal | Type: PRESCRIPTION ANIMAL DRUG LABEL
Date: 20251028

ACTIVE INGREDIENTS: PRADOFLOXACIN TRIHYDRATE 200 mg/1 mL

Elanco™

Pradalex™

(pradofloxacin injection)

200 mg pradofloxacin/mL injectable solution
Antimicrobial

CAUTION

Federal law restricts this drug to use by or on the order of a licensed veterinarian.

Federal law prohibits the extra-label use of this drug in food-producing animals.

To ensure responsible antimicrobial drug use, use of pradofloxacin should be limited to treatment of bovine respiratory disease (BRD) in cattle and treatment of swine respiratory disease (SRD) in swine only after consideration of other non-fluoroquinolone therapeutic options.

PRODUCT DESCRIPTION

Pradalex (pradofloxacin injection) is a sterile, ready-to-use injectable antimicrobial solution that contains pradofloxacin, a broad-spectrum fluoroquinolone antimicrobial agent.

Each mL of Pradalex contains 227 mg pradofloxacin trihydrate; equivalent to 200 mg of pradofloxacin. Excipients are citric acid (antioxidant) 1 mg, gluconolactone (for pH adjustment) 77 mg, and water for injection q.s. Pradofloxacin is a fluoroquinolone antimicrobial and belongs to the class of quinoline carboxylic acid derivatives. Its chemical name is 8-cyano-1-cyclopropyl-6-fluoro-7-[(4aS,7aS)-octahydro-6Hpyrrolo[3,4-b]pyridin-6-yl]-4-oxo-1,4-dihydroquinoline-3-carboxylic acid.

INDICATIONS

Cattle: Pradalex is indicated for the treatment of BRD associated with Mannheimia haemolytica, Pasteurella multocida, Histophilus somni and Mycoplasma bovis in cattle intended for slaughter (beef calves 2 months of age and older, growing beef steers, growing beef heifers, and beef bulls intended for slaughter), and in cattle intended for breeding less than 1 year of age (replacement beef and dairy heifers less than 1 year of age and beef and dairy bulls less than 1 year of age). Not for use in cattle intended for breeding 1 year of age and older (replacement beef and dairy heifers 1 year of age and older, beef and dairy bulls 1 year of age and older, and beef and dairy cows), beef calves less than 2 months of age, dairy calves, and veal calves.

Swine: Pradalex is indicated for the treatment of SRD associated with Bordetella bronchiseptica, Glaesserella (Haemophilus) parasuis, Pasteurella multocida, Streptococcus suis, and Mycoplasma hyopneumoniae in weaned swine intended for slaughter (nursery, growing, and finishing swine, boars intended for slaughter, barrows, gilts intended for slaughter, and sows intended for slaughter).

Not for use in swine intended for breeding (boars intended for breeding, replacement gilts, and sows intended for breeding) and in nursing piglets.

DOSAGE AND ADMINISTRATION

Cattle: Administer once as a subcutaneous injection at a dosage of 10 mg/kg (2.3 mL/100 lb) body weight. Do not inject more than 15 mL per subcutaneous injection site.

Table 1. Pradalex Dose Guide for Cattle (2.3 mL/100 lbs)

Weight (lb) | Dose Volume (mL)
100 | 2.3
200 | 4.6
300 | 6.9
400 | 9.2
500 | 11.5
600 | 13.8
700 | 16.1
800 | 18.4
900 | 20.7

Swine: Administer once as an intramuscular injection in the neck at a dosage of 7.5 mg/kg (1.7 mL/100 lb) body weight. Do not inject more than 5 mL per intramuscular injection site.

Table 2. Pradalex Dose Guide for Swine (1.7 mL/100 lbs)

Weight (lb) | Dose Volume (mL)
15 | 0.3
30 | 0.5
50 | 0.9
100 | 1.7
150 | 2.6
200 | 3.4
250 | 4.3

Dilution of Pradalex: Pradalex may be diluted with sterile water, sterile saline (0.9%), or 5% dextrose (D5W) prior to injection. The diluted product should be used within 24 hours. Store diluted solution in amber glass bottles between 25-40°C (77-104°F).

Table 3. Dilution Guide for Swine*

Swine Weight | mL of Pradalex | mL of diluent** | Number of doses
5 lb | 8.5 mL | 91.5 mL | 100
10 lb | 17 mL | 83 mL | 100
15 lb | 25.6 mL | 74.4 mL | 100
20 lb | 34.1 mL | 65.9 mL | 100
25 lb | 42.6 mL | 57.4 mL | 100
30 lb | 51.1 mL | 48.9 mL | 100
35 lb | 59.7 mL | 40.3 mL | 100
40 lb | 68.2 mL | 31.8 mL | 100
45 lb | 76.7 mL | 23.3 mL | 100
50 lb | 85.2 mL | 14.8 mL | 100
*For 1 mL dose volume from diluted solution
**Pradalex can be diluted with sterile water, sterile saline (0.9%), or 5% dextrose (D5W) for injection

Use bottle within 6 months of first puncture. When administering from the 250 mL bottle, puncture a maximum of 120 times. If more than 120 punctures are anticipated, the use of multi-dosing equipment is recommended. When using a draw-off spike or needle with bore diameter larger than 16-gauge, discard any product remaining in the vial immediately after use.

WITHDRAWAL PERIODS and RESIDUE WARNINGS

Cattle intended for human consumption must not be slaughtered within 4 days of treatment. Swine intended for human consumption must not be slaughtered within 2 days of treatment. Not for use in female dairy cattle 1 year of age and older, including dry dairy cows; use in these cattle may cause drug residues in milk and/or in calves born to these cows. Not for use in beef calves less than 2 months of age, dairy calves, and veal calves; a withdrawal period has not been established for this product in pre-ruminating calves.

USER SAFETY WARNINGS

Not for use in humans. Keep out of reach of children. Avoid contact with eyes and skin. In case of ocular contact, immediately remove contact lenses and flush eyes with copious amounts of water for 15 minutes. In case of dermal contact, wash skin with soap and water for at least 20 seconds. Consult a physician if irritation persists following ocular or dermal exposures, or in case of accidental ingestion. Individuals with a history of hypersensitivity to quinolones should avoid this product. In humans, there is a risk of user photosensitization within a few hours after excessive exposure to quinolones. If excessive accidental exposure occurs, avoid direct sunlight. Do not eat, drink or smoke while handling this product. To obtain a copy of the Safety Data Sheet, contact Elanco at 1-800-428-4441.

ANIMAL SAFETY WARNINGS

Not for use in animals intended for breeding because the effects of Pradalex on bovine and swine reproductive performance, pregnancy, and lactation have not been determined. Not for use in pre-ruminating calves or nursing piglets because safety and effectiveness has not been demonstrated. Swelling and inflammation may be seen at the injection site after administration. These local tissue reactions may persist beyond the slaughter withdrawal period and may result in trim loss of edible tissue at slaughter.

Quinolones should be used with caution in animals with known or suspected central nervous system (CNS) disorders. In such animals, quinolones have, in rare instances, been associated with CNS stimulation that may lead to convulsive seizures. Quinolones have been shown to produce erosions of cartilage of weightbearing joints and other signs of arthropathy in immature animals of various species. See Target Animal Safety section for additional information.

ADVERSE REACTIONS

Mild to moderate inflammatory changes of the injection site may be seen in cattle and swine treated with Pradalex.

CONTACT INFORMATION

To report suspected adverse drug experiences, for technical assistance or to obtain a copy of the Safety Data Sheet, contact Elanco at 1-800-428-4441. For additional information about reporting adverse drug experiences for animal drugs, contact FDA at 1-888-FDA-VETS or http://www.fda.gov/reportanimalae.

CLINICAL PHARMACOLOGY

Mechanism of Action

Pradofloxacin is a synthetic fluoroquinolone antibacterial drug. Pradofloxacin acts via inhibition of DNA gyrase and topoisomerase IV enzymes in bacteria to inhibit DNA and RNA synthesis. It is bactericidal with a broad spectrum of activity. As a class, fluoroquinolones are considered concentration dependent antimicrobials. Pradofloxacin induces long post-antibiotic effects (PAE) and extended post-antibiotic sub-MIC effects (PA SME), both in aerobic and anaerobic bacteria.

Pharmacokinetics

Cattle: The pharmacokinetic parameters of pradofloxacin in Table 4 were determined from two studies following subcutaneous administration of pradofloxacin in 4- to-5-month-old weaned calves weighing 158 to 319 kg.

Pradofloxacin exposure (Cmax and AUC) was dose proportional over a 10 to 50 mg/kg dose range with no accumulation when administered once every 4 days over 8 days.

Pradofloxacin was excreted in both the urine and the feces, largely unchanged, with the majority of the administered dose being excreted in the first 24 hours post-dosing.

Swine: The pharmacokinetic parameters of pradofloxacin in Table 4 were determined following intramuscular administration of pradofloxacin in 18-day-old weaned pigs weighing 5.5 to 7.9 kg. Pradofloxacin exposure (Cmax and AUC) was dose proportional over a 7.5 to 37.5 mg/kg dose range with no accumulation when administered once every 2 days over 4 days.

Pradofloxacin was excreted in both the urine and the feces, largely unchanged, with approximately one-third of the administered dose being excreted in the first 24 hours post-dosing.

Table 4. Arithmetic mean (± standard deviation) plasma pradofloxacin pharmacokinetic parameters following the first of three administrations of Pradalex (pradofloxacin injection).

Pharmacokinetic Parameter | Weaned calves (N=12) 10 mg/kg BW SC | Weaned pigs (N = 8) 7.5 mg/kg BW IM
Cmax (μg/mL) | 1.9 ± 0.4 | 2.5 ± 1.9
Tmax (hours)a | 1 (1 to 2) | 0.75 (0.5 to 2)
AUClast (hr*μg/mL) | 10.5 ± 1.2 | 26.2 ± 3.7
t1/2 (hours) | 2.8 ± 0.4b | 8.5 ± 2.6
a Reported as: Median (range)
b N=11 due to inability to calculate half-life in 1 animal
Cmax = maximum concentration
Tmax = time to maximum concentration
AUClast = area under the curve from the time of dosing to the time of the last measurable concentration
t½ = half-life

MICROBIOLOGY

Cattle: The minimal inhibitory concentrations (MICs) of pradofloxacin were determined for isolates of Mannheimia haemolytica, Pasteurella multocida, Histophilus somni, and Mycoplasma bovis which were obtained from cattle enrolled in the 2015 BRD field study conducted in the U.S. MIC determinations were completed using Clinical and Laboratory Standards Institute (CLSI) standard methods except for M. bovis. The methods and quality control performance standards for M. bovis were validated with a multi-center laboratory study. The results are shown below in Table 5.

Table 5. Pradofloxacin MIC values* of BRD pathogens isolated from the 2015 field study.

BRD Pathogens | No. of Isolates | MIC50** (μg/mL) | MIC90** (μg/mL) | MIC range (μg/mL)
M. haemolytica | 365 | 0.008 | 2 | 0.001 to 2
P. multocida | 248 | 0.008 | 0.015 | 0.001 to 0.12
H. somni | 106 | 0.015 | 0.015 | 0.015 to 0.25
M. bovis | 159 | 0.12 | 0.5 | 0.002 to 1
* The correlation between in vitro susceptibility data and clinical effectiveness is unknown.
** The lowest MIC to encompass 50% and 90% of the most susceptible isolates, respectively.

Swine: The MICs of pradofloxacin were determined for isolates of Bordetella bronchiseptica, Glaesserella (Haemophilus) parasuis, Pasteurella multocida and Streptococcus suis which were obtained from swine enrolled in the 2017 SRD field study conducted in the U.S. MIC determinations were completed using CLSI standard methods except for G. parasuis. The methods for G. parasuis were validated with a multi-center laboratory study. The results are shown below in Table 6.

Table 6. Pradofloxacin MIC values* of SRD pathogens isolated from the 2017 field study.

SRD Pathogens | No. of Isolates | MIC50** (μg/mL) | MIC90** (μg/mL) | MIC range (μg/mL)
B. bronchiseptica | 111 | 0.12 | 0.12 | 0.12 to 0.25
G. parasuis | 93 | 0.001 | 0.004 | 0.00025 to 0.008
P. multocida | 99 | 0.004 | 0.008 | 0.004 to 0.008
S. suis | 212 | 0.06 | 0.25 | 0.015 to 4
* The correlation between in vitro susceptibility data and clinical effectiveness is unknown.
** The lowest MIC to encompass 50% and 90% of the most susceptible isolates, respectively.

EFFECTIVENESS

Cattle: The effectiveness of Pradalex for the treatment of BRD associated with Mannheimia haemolytica, Pasteurella multocida, Histophilus somni and Mycoplasma bovis was demonstrated in a multi-site natural infection field study conducted in the U.S. A total of 630 commercial, mixed-breed male and female calves with clinical BRD were enrolled. Calves were administered a single subcutaneous dose of either Pradalex at 10 mg/kg body weight or an equivalent volume of sterile saline. Calves were evaluated for clinical success on Day 10. The success rate of Pradalex-treated calves (49.7%) was statistically significantly different (p = 0.0089) and numerically greater than that of saline-treated calves (25.6%) (based on back-transformed least squares means). No adverse events associated with Pradalex administration were reported in the study.

Swine: The effectiveness of Pradalex for the treatment of SRD associated with Bordetella bronchiseptica, Glaesserella (Haemophilus) parasuis, Pasteurella multocida, Streptococcus suis, and Mycoplasma hyopneumoniae was demonstrated in a multi-site, natural infection field study conducted in the U.S. A total of 1,200 castrated male and female growing pigs with clinical SRD were enrolled. At enrollment, pigs were administered a single intramuscular dose of either Pradalex at 7.5 mg/kg body weight, or an equivalent volume of sterile saline. Pigs were evaluated for clinical success on Day 7. The success rate of Pradalex-treated pigs (45.2%) was statistically significantly different (p=0.0274) and numerically greater than that of the saline-treated pigs (34.2%) (based on least squares means). No adverse events associated with Pradalex administration were reported in the study.

A total of 72 castrated male and female growing pigs were enrolled in an M. hyopneumoniae-induced challenge model study. Pigs were inoculated with a field strain of M. hyopneumoniae once daily for three consecutive days. Three days after the final inoculation, pigs were administered a single intramuscular dose of either Pradalex at 7.5 mg/kg body weight, or an equivalent volume of sterile saline. Pigs were euthanized and necropsied on Day 10. There was a significant difference (p=0.0002) in the mean total lung lesion score in favor of Pradalex-treated pigs (11.7%) compared to the saline-treated pigs (33.1%).

TARGET ANIMAL SAFETY

Cattle: Pradalex was evaluated in a margin of safety study with 32 healthy, weaned calves. Calves were randomized to four treatment groups: 0X (saline control), 1X (10 mg pradofloxacin/kg), 3X (30 mg pradofloxacin/kg) and 5X (50 mg pradofloxacin/kg). Calves were administered subcutaneous doses on Days 0, 4, and 8. All calves remained clinically normal throughout the in-life study and survived until scheduled necropsy on Day 9. Injection site swelling was noted in the 1X and 5X groups. Neutrophil counts, monocyte counts, and creatine kinase levels were generally higher in the treated groups, and this was attributed to inflammation and tissue damage at the injection sites. At necropsy, injection site lesions consisting of discoloration and edema, with microscopically visible hemorrhage, inflammation, and necrosis were reported in most treated animals. No signs of fluoroquinolone-induced arthropathy were reported. No other clinically significant adverse effects related to Pradalex were reported.

Pradalex was also evaluated in a margin of safety study focusing on pathologic changes to the testes and epididymides in 16 healthy, weaned bull calves. Calves were randomized to four treatment groups: 0X (saline control), 1X (10 mg pradofloxacin/kg), 3X (30 mg pradofloxacin/kg) and 5X (50 mg pradofloxacin/kg). Calves were administered subcutaneous doses on Days 0, 4, and 8. All calves remained clinically normal throughout the study and survived until scheduled castration on Day 9. Injection site swelling was noted in the 1X, 3X, and 5X groups. In the 1X group, 3 of 4 calves developed mild to moderate subcutaneous swellings, one resolved by 6 hours post-treatment and two were not resolved by the end of the study. No abnormal macroscopic or microscopic pathology in the testes or epididymides was reported.

Swine: Pradalex was evaluated in a margin of safety study with 32 healthy, weaned, crossbred pigs. Pigs were randomized to four treatment groups: 0X (saline control), 1X (7.5 mg pradofloxacin/kg), 3X (22.5 mg pradofloxacin/kg) and 5X (37.3mg pradofloxacin/kg). Pigs were administered intramuscular doses on Days 0, 2, and 4. All pigs remained clinically normal throughout the in-life study and all pigs survived until scheduled necropsy on Day 11. Aspartate aminotransferase (AST) and creatine phosphokinase (CK) showed elevations and statistically significant treatment by day interactions in Pradalex-treated pigs. These were attributed to inflammation and tissue damage at the injection sites and the values returned to normal by Day 10. There were no other clinically relevant effects on the remaining clinical pathology results. At necropsy, the only macroscopic and microscopic lesions attributable to Pradalex were related to tissue injury at the intramuscular injection sites. No signs of fluoroquinolone-induced arthropathy were reported. No other clinically significant adverse effects related to Pradalex were reported.

STORAGE CONDITIONS

Protect from direct sunlight. Do not refrigerate or freeze. Store at 25ºC (77ºF), excursions permitted up to 40ºC (104ºF) and down to -20ºC (-4ºF).

See in-use instructions provided in the Dosage and Administration section.

HOW SUPPLIED

200 mg/mL 250 mL bottles
200 mg/mL 100 mL bottles

Pradalex is protected by one or more U.S. patents: see patent information at http://www.elancopatents.com

Approved by FDA under NADA # 141-550

Pradalex, Elanco and the diagonal bar logo are trademarks of Elanco or its affiliates.

© 2025 Elanco or its affiliates

Product of Germany

Manufactured for: Elanco US Inc. Indianapolis, IN 46221

Revision August 2025

ElancoTM

PA600570X

Principal Display Panel – 100 mL Labels

Elanco™

Pradalex™
(pradofloxacin injection)

Injectable Solution
Antimicrobial

200 mg of pradofloxacin/mL

Net Contents: 100 mL

Approved by FDA under NADA # 141-550

Elanco

Pradalex™
(pradofloxacin injection)

Injectable Solution
Antimicrobial
200 mg of pradofloxacin/mL

Net Contents: 100 mL Approved by FDA under NADA # 141-550

Principal Display Panel – 250 mL Labels

Elanco™

Pradalex™
(pradofloxacin injection)

Injectable Solution
Antimicrobial

200 mg of pradofloxacin/mL

Net Contents: 250 mL

Approved by FDA under NADA # 141-550

Elanco™

Pradalex™
(pradofloxacin injection)

Injectable Solution
Antimicrobial
200 mg of pradofloxacin/mL

Net Contents: 250 mL

Approved by FDA under NADA # 141-550